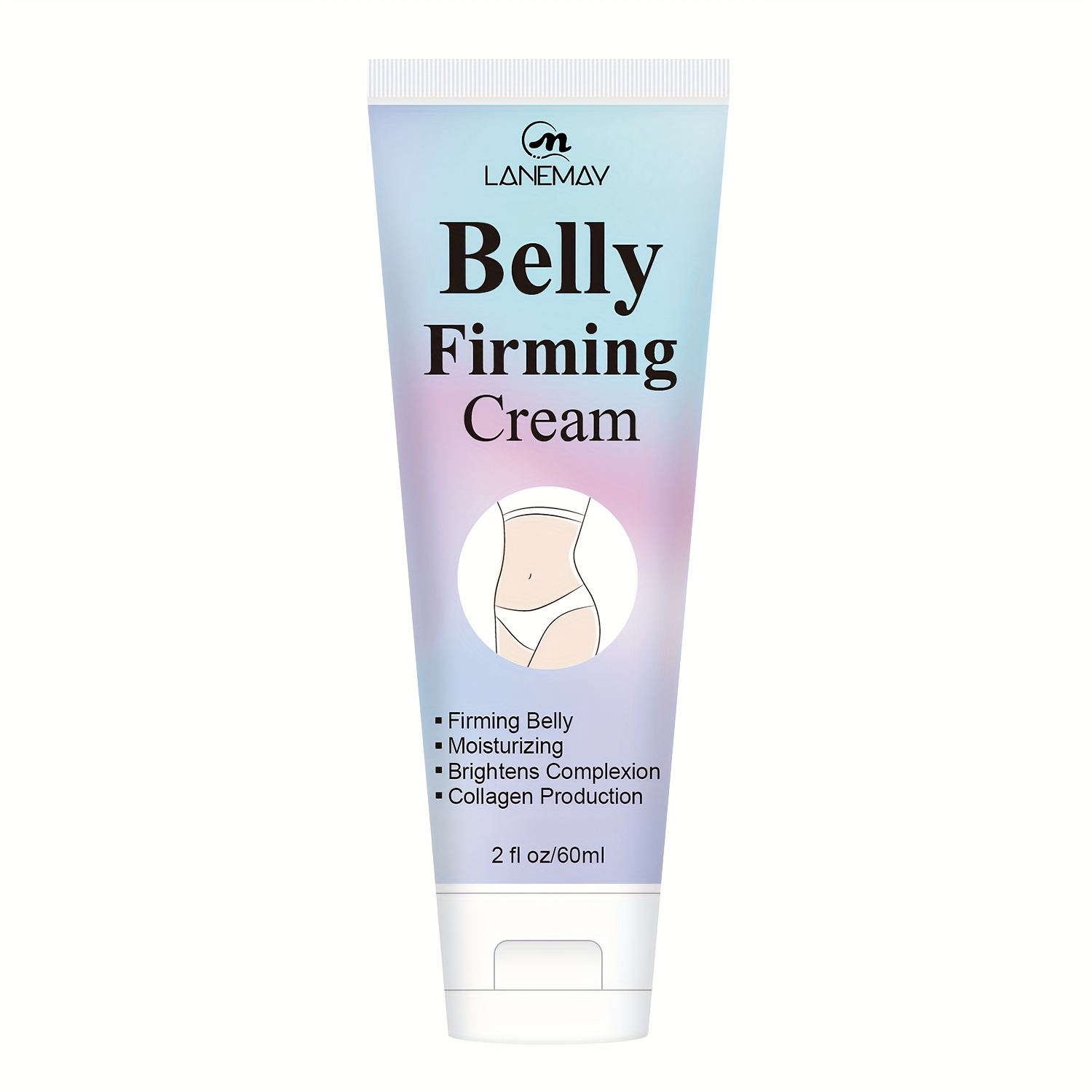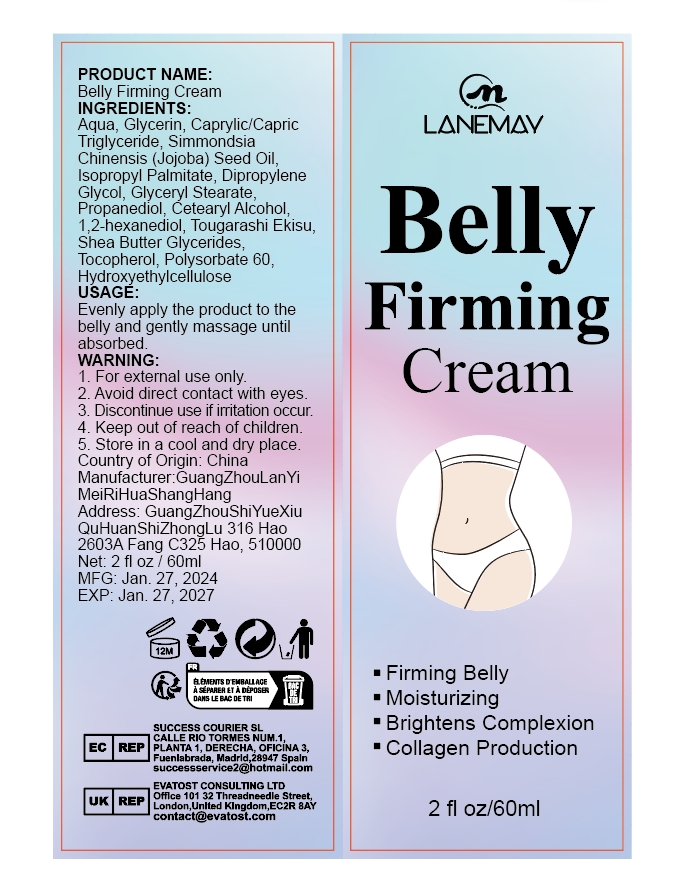 DRUG LABEL: Belly Firming Cream
NDC: 84025-024 | Form: CREAM
Manufacturer: Guangzhou Yanxi Biotechnology Co., Ltd
Category: otc | Type: HUMAN OTC DRUG LABEL
Date: 20240329

ACTIVE INGREDIENTS: ISOPROPYL PALMITATE 100 mg/1 mL; GLYCERIN 100 mg/1 mL
INACTIVE INGREDIENTS: WATER

DOSAGE AND ADMINISTRATION

use as a normal body cream

WARNINGS

For external use only. Keep out of reach of children.

INACTIVE INGREDIENT

Aqua

Keep out of Children

PURPOSE

Helps tighten the skin

INDICATIONS AND USAGE

Evenly apply the product to the belly and gently massage until absorbed.